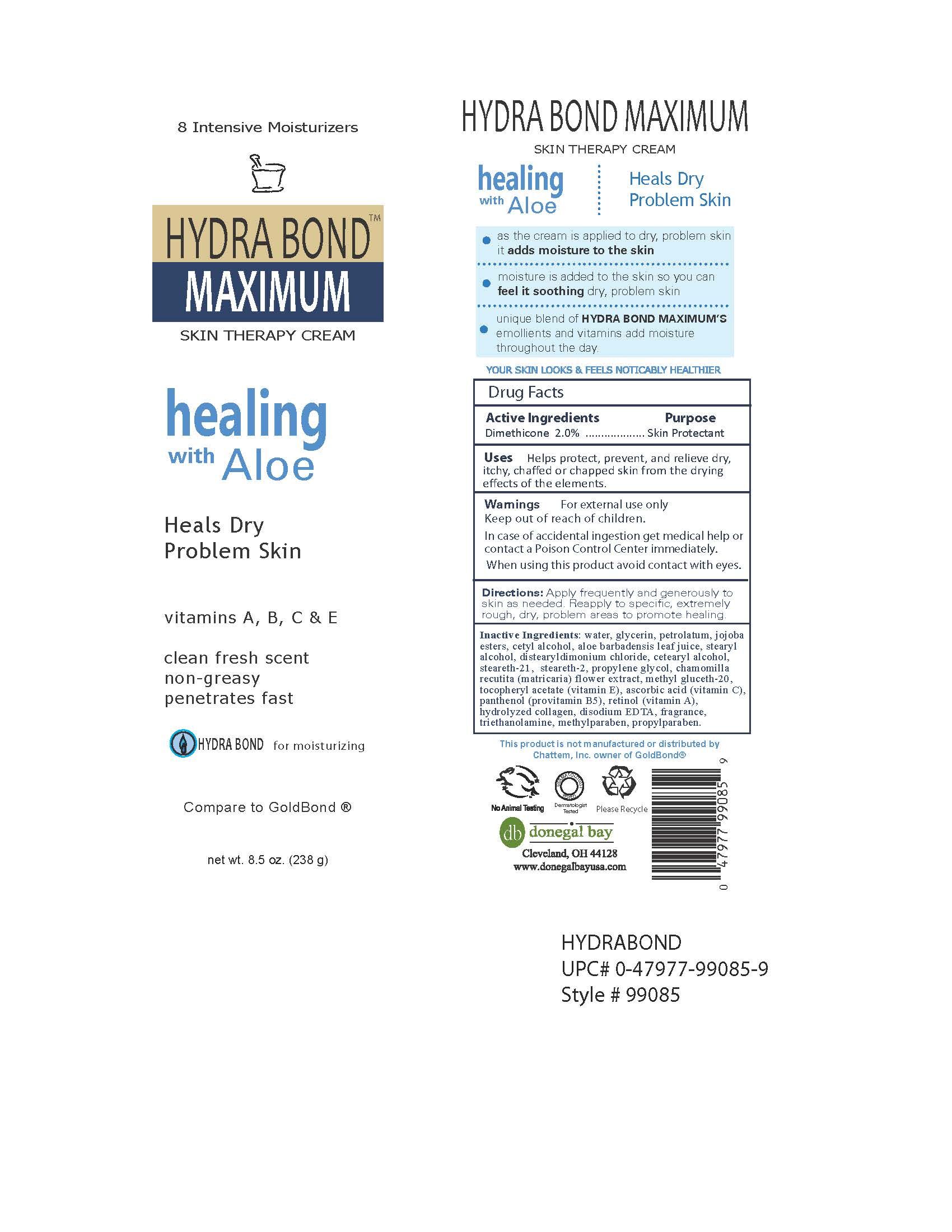 DRUG LABEL: Hydra Bond Maximum Skin Therapy Cream
NDC: 70990-004 | Form: CREAM
Manufacturer: Donegal Bay Ltd
Category: otc | Type: HUMAN OTC DRUG LABEL
Date: 20161012

ACTIVE INGREDIENTS: DIMETHICONE 2 g/100 mL
INACTIVE INGREDIENTS: WATER; GLYCERIN; PETROLATUM; ALOE VERA LEAF; STEARYL ALCOHOL; DISTEARYLDIMONIUM CHLORIDE; CETYL ALCOHOL; STEARETH-21; STEARETH-2; PROPYLENE GLYCOL; MATRICARIA RECUTITA FLOWERING TOP; METHYL GLUCETH-20; .ALPHA.-TOCOPHEROL ACETATE; METHYLPARABEN; PROPYLPARABEN; ASCORBIC ACID; PANTHENOL; RETINOL; DISODIUM HEDTA; TRIETHANOLAMINE LAURATE

Daily Moisturizing Lotion

Active Ingredient:

Dimethicone 2.0%

Purpose:

Skin Protectant

Uses:

Helps protect, prevent, and relieve dry, itchy, chaffed or chapped skin from the drying effects of the elements.

Warnings:

For external use only

When using this product, avoid contacting with eyes

STOP USE

In case of accidental ingestion get medical help or contact a Poison Control Center immediately.

Keep out of reach of children.

Directions:

Apply frequently and generously to skin as needed. Reapply to specific. extremely rough, dry, problem area to promote healing.

Inactive Ingredients:

Water, Glycerin, Petrolatum, Jojoba Ester, Cetyl Alcohol, Aloe Barbadensis Leaf Juice, Stearyl Alcohol, Distearyldimonium Chloride, Cetearyl Alcohol, Steareth-21, Steareth-2, Propylene Glycol, Chamomilla Recutita (Matricaria) Flower Extract, Methyl Glueth-20, Tocopheryl Acetate (Vitamin E), Ascorbic Acid (Vitamin C), Panthenol (Vitamin B5), Retinol (Vitamin A), Hydrolyzed Collagen, Disodium EDTA, Fragrance, triethanolamine, Methylparaben, Propylparaben